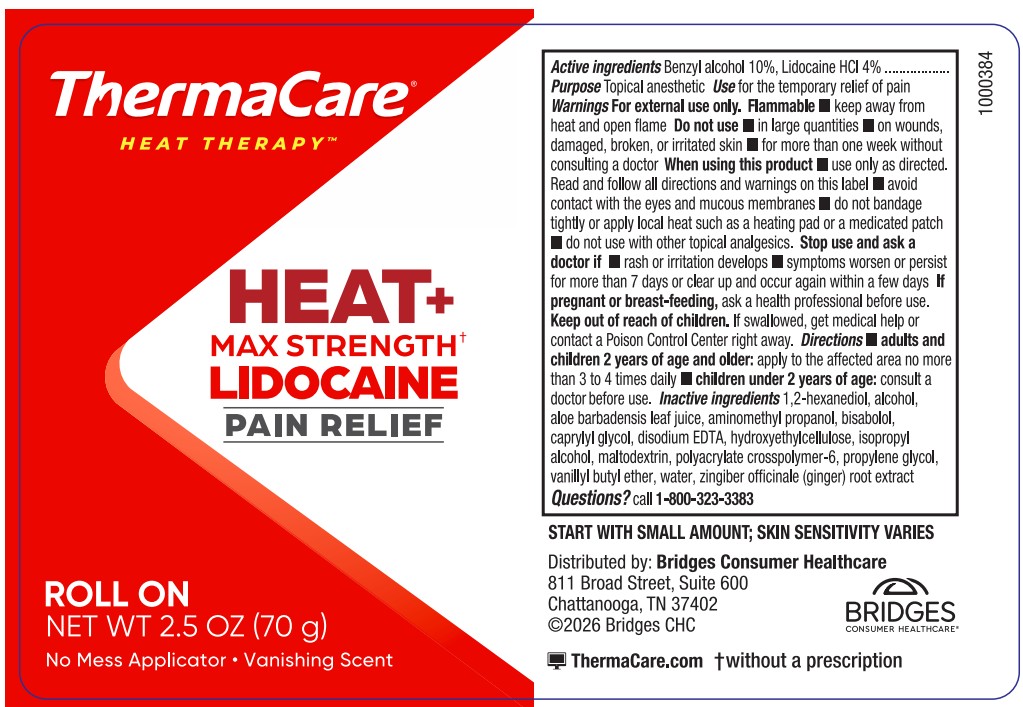 DRUG LABEL: Thermacare Heat Therapy Max Strength Lidocaine Pain Relief Rollon
NDC: 69693-002 | Form: LIQUID
Manufacturer: Clarion Brands LLC
Category: otc | Type: HUMAN OTC DRUG LABEL
Date: 20251126

ACTIVE INGREDIENTS: LIDOCAINE HYDROCHLORIDE 4 g/100 mL; BENZYL ALCOHOL 10 g/100 mL
INACTIVE INGREDIENTS: POLYACRYLATE CROSSPOLYMER-6; VANILLYL BUTYL ETHER; PROPYLENE GLYCOL; CAPRYLYL GLYCOL; 1,2-HEXANEDIOL; EDETATE DISODIUM; HYDROXYETHYLCELLULOSE; WATER; BISABOLOL; ALOE BARBADENSIS LEAF JUICE; AMINOMETHYLPROPANOL; GINGER; ALCOHOL; MALTODEXTRIN

ACTIVE INGREDIENT

Benzyl alcohol 10%

Lidocaine HCl 4%

PURPOSE

Topical anesthetic

INDICATIONS AND USAGE

Use for the temporary relief of pain

WARNINGS

For external use only

Flammable keep away from heat and open flame

Do not use

- in large quantities
- on wounds, damaged, broken, or irritated skin
- for more than one week without consulting a doctor

When using this product

- use only as directed. Read and follow all directions and warnings on this label
- avoid contact with the eyes and mucous membranes
- do not bandage tightly or apply local heat such as a heating pad or a medicated patch
- do not use with other topical analgesics

Stop use and ask a doctor if

- rash or irritation develops
- symptoms worsen or persist for more than 7 days or clear up and occur again within a few days

If pregnant or breast-feeding, ask a health professional before use.

Keep out of reach of children. If swallowed, get medical help or contact a Poison Control Center right away.

WHEN USING

- adults and children 2 years of age and older: apply to the affected area no more than 3 to 4 times daily
- children under 2 years of age: consult a doctor before use

INACTIVE INGREDIENT

1, 2 hexanediol

alcohol

aloe barbadensis leaf juice

aminomethyl propanol

bisabolol

caprylyl glycol

disodium EDTA

hydroxyethylcellulose

isopropyl alcohol

maltodextrin

polyacrylate crosspolyer-6

propylene glycol

vanillyl butyl ether

water

zingiber officinale (ginger) root extract

QUESTIONS

1-800-323-3383

DOSAGE AND ADMINISTRATION

Benzyl alcohol 10%

Lidocaine HCl 4%

Directions

adults and children 2 years of age and older: apply to affected area no more than 3 to 4 times daily
children under 2 years of age: consult a doctor before use.

PACKAGE LABEL

Thermacare Heat Therapy

Heat + Max Strength Lidocaine Pain Relief

Roll On NET WT 2.5 OZ (70 g)

No Mess Applicator

Vanishing Scent

Start with Small Amount; Skin Sensitivity Varies

Distributed by: Bridges Consumer Healthcare

811 Broad Street, Suite 600

Chattanooga, TN 37402

2026 Bridges CHC

Thermacare.com